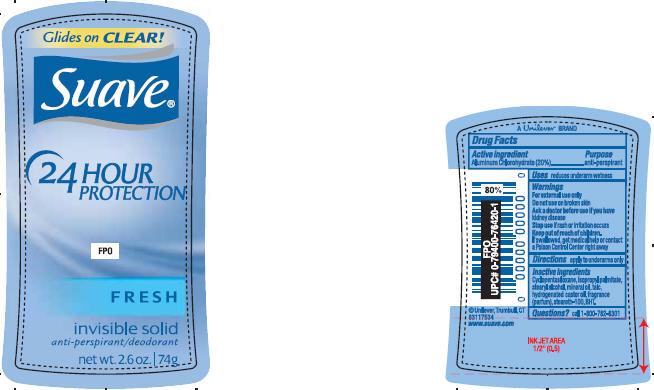 DRUG LABEL: Suave Fresh
NDC: 64942-0774 | Form: STICK
Manufacturer: Conopco Inc. d/b/a Unilever
Category: otc | Type: HUMAN OTC DRUG LABEL
Date: 20100511

ACTIVE INGREDIENTS: Aluminum Chlorohydrate 20 g/100 g

PDP and Drug facts box text for Suave Fresh Antiperspirant and Deodorant

Active ingredient Purpose

Aluminum Chlorohydrate (20%).......................................antiperspirant

WARNINGS

For external use only

Do not use on broken skin

Ask a doctor before use if you have kidney disease

Stop use if rash or irritation occurs

Keep out of reach of children. If swallowed, get medical help or contact a Poison Control Center right away.

Inactive Ingredients
Cyclopentasiloxane, Isopropyl Palmitate, Stearyl Alcohol, Mineral Oil, Talc, Hydrogenated Castor Oil, Fragrance (Parfum), Steareth-100, BHT.

Questions?
Call 1-800-782-8301

PACKAGE LABEL

PDP 2.6 oz